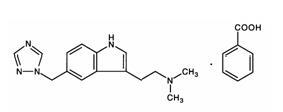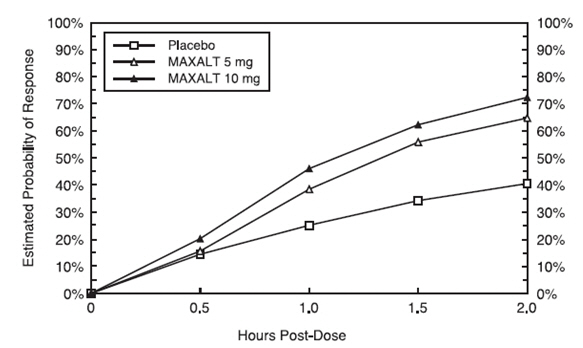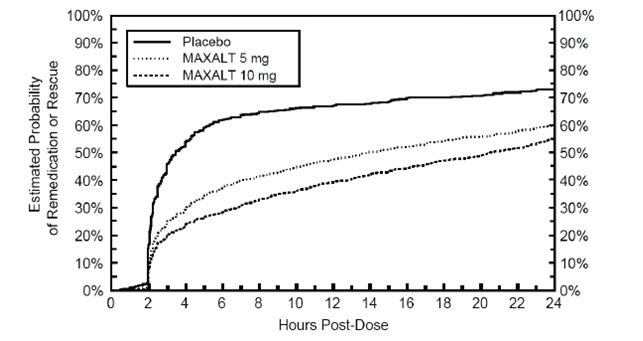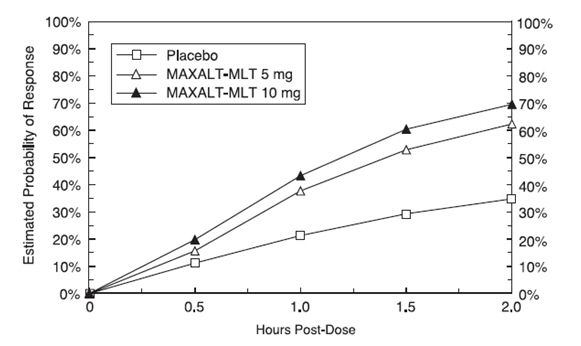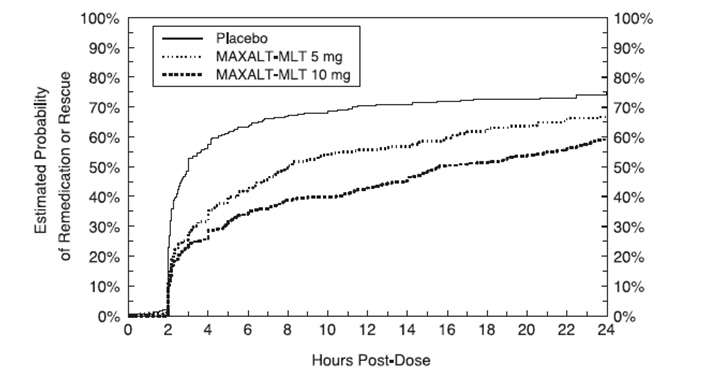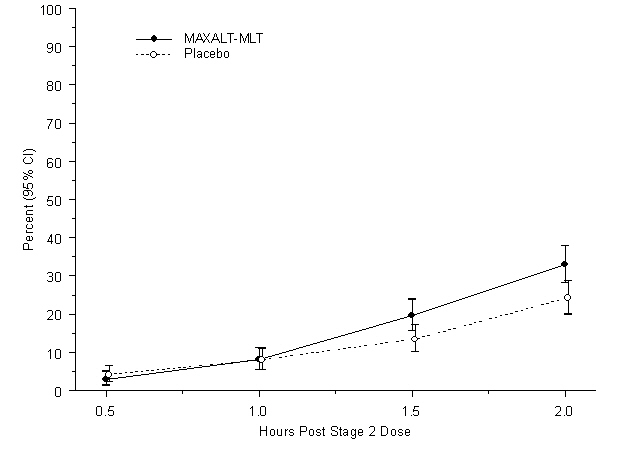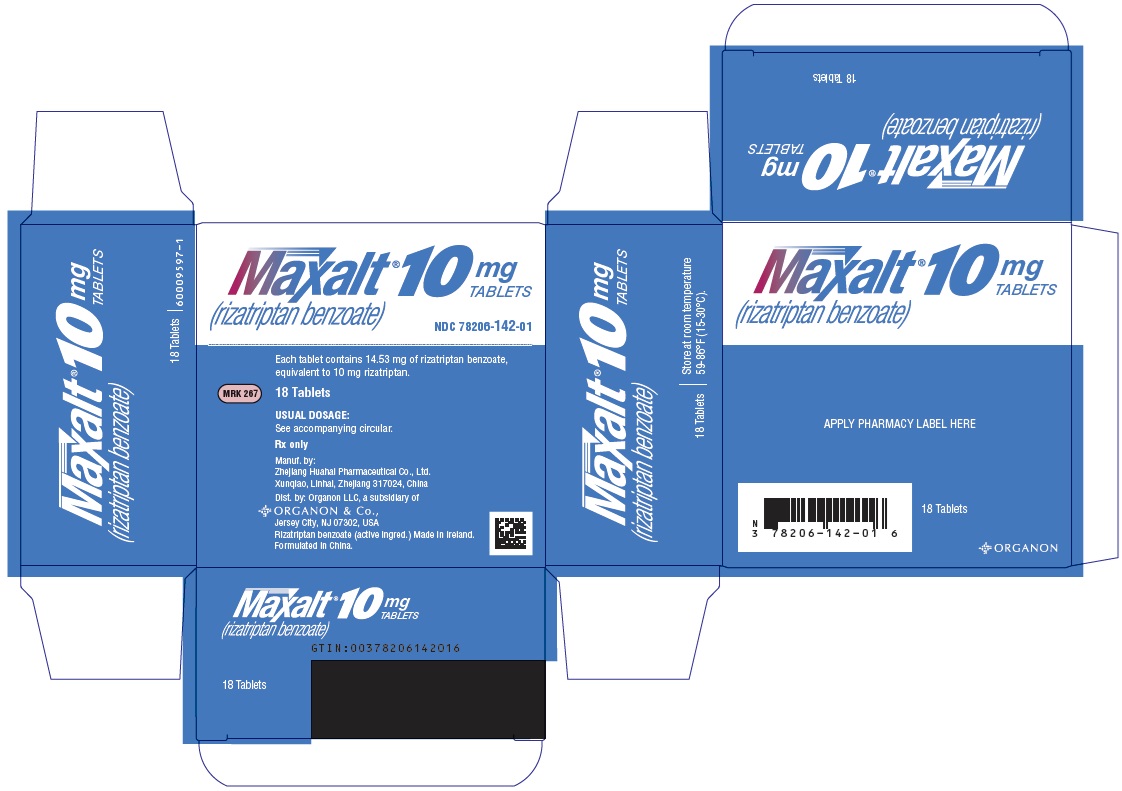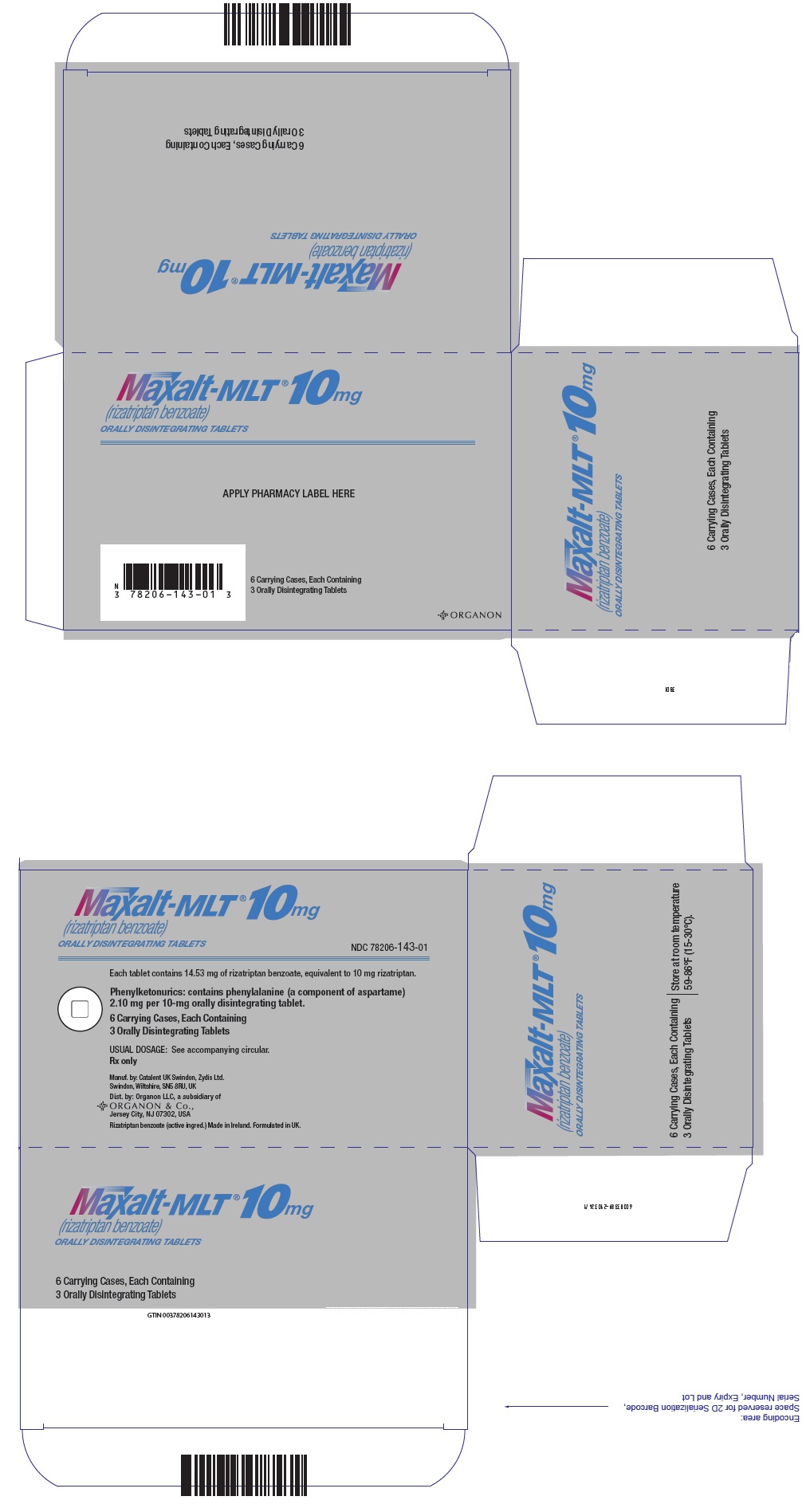 DRUG LABEL: MAXALT
NDC: 78206-142 | Form: TABLET
Manufacturer: Organon LLC
Category: prescription | Type: HUMAN PRESCRIPTION DRUG LABEL
Date: 20260129

ACTIVE INGREDIENTS: rizatriptan benzoate 10 mg/1 1
INACTIVE INGREDIENTS: lactose monohydrate; MICROCRYSTALLINE CELLULOSE; STARCH, CORN; FERRIC OXIDE RED; magnesium stearate

HIGHLIGHTS OF PRESCRIBING INFORMATION

These highlights do not include all the information needed to use MAXALT and MAXALT-MLT safely and effectively. See full prescribing information for MAXALT and MAXALT-MLT.
MAXALT® (rizatriptan benzoate) tablets, for oral use
MAXALT-MLT® (rizatriptan benzoate) orally disintegrating tablets
Initial U.S. Approval: 1998

RECENT MAJOR CHANGES

Dosage and Administration (2) | 09/2020

1 INDICATIONS AND USAGE

MAXALT is a serotonin (5-HT) 1B/1D receptor agonist (triptan) indicated for the acute treatment of migraine with or without aura in adults and in pediatric patients 6 to 17 years of age (1)

Limitations of Use:

- Use only after clear diagnosis of migraine has been established (1)
- Not indicated for the prophylactic therapy of migraine (1)
- Not indicated for the treatment of cluster headache (1)

2 DOSAGE AND ADMINISTRATION

- Adults: 5 or 10 mg single dose; separate repeat doses by at least two hours; maximum dose in a 24-hour period: 30 mg (2.1)
- Pediatric patients 6 to 17 years: 5 mg single dose in patients less than 40 kg (88 lb); 10 mg single dose in patients 40 kg (88 lb) or more (2.2)
- Adjust dose if co-administered with propranolol (2.4)

3 DOSAGE FORMS AND STRENGTHS

- MAXALT Tablets: 10 mg (3)
- MAXALT-MLT Orally Disintegrating Tablets: 10 mg (3)

4 CONTRAINDICATIONS

- History of ischemic heart disease or coronary artery vasospasm (4)
- History of stroke or transient ischemic attack (4)
- Peripheral vascular disease (4)
- Ischemic bowel disease (4)
- Uncontrolled hypertension (4)
- Recent (within 24 hours) use of another 5-HT1 agonist (e.g., another triptan), or of an ergotamine-containing medication (4)
- Hemiplegic or basilar migraine (4)
- MAO-A inhibitor used in the past 2 weeks (4)
- Hypersensitivity to rizatriptan or any of the excipients (4)

5 WARNINGS AND PRECAUTIONS

- Myocardial ischemia, myocardial infarction, and Prinzmetal's angina: Perform cardiac evaluation in patients with multiple cardiovascular risk factors (5.1)
- Arrhythmias: Discontinue dosing if occurs (5.2)
- Chest/throat/neck/jaw pain, tightness, pressure, or heaviness; Generally not associated with myocardial ischemia; Evaluate patients at high risk (5.3)
- Cerebral hemorrhage, subarachnoid hemorrhage, and stroke: Discontinue dosing if occurs (5.4)
- Gastrointestinal ischemic events, peripheral vasospastic reactions: Discontinue dosing if occurs (5.5)
- Medication overuse headache: Detoxification may be necessary (5.6)
- Serotonin syndrome: Discontinue dosing if occurs (5.7)

6 ADVERSE REACTIONS

The most common adverse reactions in adults were (incidence ≥5% and greater than placebo): asthenia/fatigue, somnolence, pain/pressure sensation and dizziness (6.1)

To report SUSPECTED ADVERSE REACTIONS, contact Organon LLC, a subsidiary of Organon & Co., at 1-844-674-3200 or FDA at 1-800-FDA-1088 or www.fda.gov/medwatch.

8 USE IN SPECIFIC POPULATIONS

- Pregnancy: Based on animal data, may cause fetal harm (8.1)
- Phenylketonurics: MAXALT-MLT contains phenylalanine (8.6)

FULL PRESCRIBING INFORMATION

1 INDICATIONS AND USAGE

MAXALT® and MAXALT-MLT® are indicated for the acute treatment of migraine with or without aura in adults and in pediatric patients 6 to 17 years old.

Limitations of Use

- MAXALT should only be used where a clear diagnosis of migraine has been established. If a patient has no response for the first migraine attack treated with MAXALT, the diagnosis of migraine should be reconsidered before MAXALT is administered to treat any subsequent attacks.
- MAXALT is not indicated for use in the management of hemiplegic or basilar migraine [see Contraindications (4)].
- MAXALT is not indicated for the prevention of migraine attacks.
- Safety and effectiveness of MAXALT have not been established for cluster headache.

2 DOSAGE AND ADMINISTRATION

Although rizatriptan benzoate 5 mg tablets and orally disintegrating tablets are available in the marketplace, MAXALT Tablets and MAXALT-MLT Orally Disintegrating Tablets are no longer marketed in the 5 mg strength.

2.1 Dosing Information in Adults

The recommended starting dose of rizatriptan benzoate is either 5 mg or 10 mg for the acute treatment of migraines in adults. The 10-mg dose may provide a greater effect than the 5-mg dose, but may have a greater risk of adverse reactions [see Clinical Studies (14.1)].

Redosing in Adults

Although the effectiveness of a second dose or subsequent doses has not been established in placebo-controlled trials, if the migraine headache returns, a second dose may be administered 2 hours after the first dose. The maximum daily dose should not exceed 30 mg in any 24-hour period. The safety of treating, on average, more than four headaches in a 30-day period has not been established.

2.2 Dosing Information in Pediatric Patients (Age 6 to 17 Years)

Dosing in pediatric patients is based on the patient's body weight. The recommended dose of rizatriptan benzoate is 5 mg in patients weighing less than 40 kg (88 lb), and 10 mg in patients weighing 40 kg (88 lb) or more.

The efficacy and safety of treatment with more than one dose of rizatriptan benzoate within 24 hours in pediatric patients 6 to 17 years of age have not been established.

2.3 Administration of MAXALT-MLT Orally Disintegrating Tablets

For MAXALT-MLT Orally Disintegrating Tablets, administration with liquid is not necessary. Orally disintegrating tablets are packaged in a blister within an outer aluminum pouch and patients should not remove the blister from the outer pouch until just prior to dosing. The blister pack should then be peeled open with dry hands and the orally disintegrating tablet placed on the tongue, where it will dissolve and be swallowed with the saliva.

2.4 Dosage Adjustment for Patients on Propranolol

Adult Patients

In adult patients taking propranolol, only the 5-mg dose of rizatriptan benzoate is recommended, up to a maximum of 3 doses in any 24-hour period (15 mg) [see Drug Interactions (7.1) and Clinical Pharmacology (12.3)].

Pediatric Patients

For pediatric patients weighing 40 kg (88 lb) or more, taking propranolol, only a single 5-mg dose of rizatriptan benzoate is recommended (maximum dose of 5 mg in a 24-hour period). Rizatriptan benzoate should not be prescribed to propranolol-treated pediatric patients who weigh less than 40 kg (88 lb) [see Drug Interactions (7.1) and Clinical Pharmacology (12.3)].

3 DOSAGE FORMS AND STRENGTHS

MAXALT Tablets

- 10 mg tablets are pale pink, capsule-shaped, compressed tablets coded MAXALT on one side and MRK 267 on the other.

MAXALT-MLT Orally Disintegrating Tablets

- 10 mg orally disintegrating tablets are white to off-white, round lyophilized tablets debossed with a modified square on one side.

4 CONTRAINDICATIONS

MAXALT is contraindicated in patients with:

- Ischemic coronary artery disease (angina pectoris, history of myocardial infarction, or documented silent ischemia), or other significant underlying cardiovascular disease [see Warnings and Precautions (5.1)].
- Coronary artery vasospasm including Prinzmetal's angina [see Warnings and Precautions (5.1)].
- History of stroke or transient ischemic attack (TIA) [see Warnings and Precautions (5.4)].
- Peripheral vascular disease (PVD) [see Warnings and Precautions (5.5)].
- Ischemic bowel disease [see Warnings and Precautions (5.5)].
- Uncontrolled hypertension [see Warnings and Precautions (5.8)].
- Recent use (i.e., within 24 hours) of another 5-HT1 agonist, ergotamine-containing medication, or ergot-type medication (such as dihydroergotamine or methysergide) [see Drug Interactions (7.2 and 7.3)].
- Hemiplegic or basilar migraine [see Indications and Usage (1)].
- Concurrent administration or recent discontinuation (i.e., within 2 weeks) of a MAO-A inhibitor [see Drug Interactions (7.5) and Clinical Pharmacology (12.3)].
- Hypersensitivity to rizatriptan or any of the excipients (angioedema and anaphylaxis seen) [see Adverse Reactions (6.2)].

5 WARNINGS AND PRECAUTIONS

5.1 Myocardial Ischemia, Myocardial Infarction, and Prinzmetal's Angina

MAXALT should not be given to patients with ischemic or vasospastic coronary artery disease. There have been rare reports of serious cardiac adverse reactions, including acute myocardial infarction, occurring within a few hours following administration of MAXALT. Some of these reactions occurred in patients without known coronary artery disease (CAD). 5-HT1 agonists, including MAXALT may cause coronary artery vasospasm (Prinzmetal's Angina), even in patients without a history of CAD.

Triptan-naïve patients who have multiple cardiovascular risk factors (e.g., increased age, diabetes, hypertension, smoking, obesity, strong family history of CAD) should have a cardiovascular evaluation prior to receiving MAXALT. If there is evidence of CAD or coronary artery vasospasm, MAXALT should not be administered [see Contraindications (4)]. For patients who have a negative cardiovascular evaluation, consideration should be given to administration of the first MAXALT dose in a medically-supervised setting and performing an electrocardiogram (ECG) immediately following MAXALT administration. Periodic cardiovascular evaluation should be considered in intermittent long-term users of MAXALT who have cardiovascular risk factors.

5.2 Arrhythmias

Life-threatening disturbances of cardiac rhythm, including ventricular tachycardia and ventricular fibrillation leading to death, have been reported within a few hours following the administration of 5-HT1 agonists. Discontinue MAXALT if these disturbances occur.

5.3 Chest, Throat, Neck and/or Jaw Pain/Tightness/Pressure

As with other 5-HT1 agonists, sensations of tightness, pain, pressure, and heaviness in the precordium, throat, neck and jaw commonly occur after treatment with MAXALT and are usually non-cardiac in origin. However, if a cardiac origin is suspected, patients should be evaluated. Patients shown to have CAD and those with Prinzmetal's variant angina should not receive 5-HT1 agonists.

5.4 Cerebrovascular Events

Cerebral hemorrhage, subarachnoid hemorrhage, and stroke have occurred in patients treated with 5-HT1 agonists, and some have resulted in fatalities. In a number of cases, it appears possible that the cerebrovascular events were primary, the 5-HT1 agonist having been administered in the incorrect belief that the symptoms experienced were a consequence of migraine, when they were not. Also, patients with migraine may be at increased risk of certain cerebrovascular events (e.g., stroke, hemorrhage, transient ischemic attack). Discontinue MAXALT if a cerebrovascular event occurs.

As with other acute migraine therapies, before treating headaches in patients not previously diagnosed as migraineurs, and in migraineurs who present with atypical symptoms, care should be taken to exclude other potentially serious neurological conditions. MAXALT should not be administered to patients with a history of stroke or transient ischemic attack [see Contraindications (4)].

5.5 Other Vasospasm Reactions

5-HT1 agonists, including MAXALT, may cause non-coronary vasospastic reactions, such as peripheral vascular ischemia, gastrointestinal vascular ischemia and infarction (presenting with abdominal pain and bloody diarrhea), splenic infarction, and Raynaud's syndrome. In patients who experience symptoms or signs suggestive of non-coronary vasospasm reaction following the use of any 5-HT1 agonist, the suspected vasospasm reaction should be ruled out before receiving additional MAXALT doses.

Reports of transient and permanent blindness and significant partial vision loss have been reported with the use of 5-HT1 agonists. Since visual disorders may be part of a migraine attack, a causal relationship between these events and the use of 5-HT1 agonists have not been clearly established.

5.6 Medication Overuse Headache

Overuse of acute migraine drugs (e.g., ergotamine, triptans, opioids, or a combination of drugs for 10 or more days per month) may lead to exacerbation of headache (medication overuse headache). Medication overuse headache may present as migraine-like daily headaches, or as a marked increase in frequency of migraine attacks. Detoxification of patients, including withdrawal of the overused drugs, and treatment of withdrawal symptoms (which often includes a transient worsening of headache) may be necessary.

5.7 Serotonin Syndrome

Serotonin syndrome may occur with triptans, including MAXALT particularly during co-administration with selective serotonin reuptake inhibitors (SSRIs), serotonin norepinephrine reuptake inhibitors (SNRIs), tricyclic antidepressants (TCAs), and MAO inhibitors [see Drug Interactions (7.5)]. Serotonin syndrome symptoms may include mental status changes (e.g., agitation, hallucinations, coma), autonomic instability (e.g., tachycardia, labile blood pressure, hyperthermia), neuromuscular aberrations (e.g., hyperreflexia, incoordination) and/or gastrointestinal symptoms (e.g., nausea, vomiting, diarrhea). The onset of symptoms can occur within minutes to hours of receiving a new or a greater dose of a serotonergic medication. MAXALT treatment should be discontinued if serotonin syndrome is suspected [see Drug Interactions (7.4) and Patient Counseling Information (17)].

5.8 Increase in Blood Pressure

Significant elevation in blood pressure, including hypertensive crisis with acute impairment of organ systems, has been reported on rare occasions in patients with and without a history of hypertension receiving 5-HT1 agonists, including MAXALT. In healthy young adult male and female patients who received maximal doses of MAXALT (10 mg every 2 hours for 3 doses), slight increases in blood pressure (approximately 2-3 mmHg) were observed. MAXALT is contraindicated in patients with uncontrolled hypertension [see Contraindications (4)].

6 ADVERSE REACTIONS

The following adverse reactions are discussed in more detail in other sections of the labeling:

- Myocardial Ischemia, Myocardial Infarction, and Prinzmetal's Angina [see Warnings and Precautions (5.1)].
- Arrhythmias [see Warnings and Precautions (5.2)].
- Chest, Throat, Neck and/or Jaw Pain/Tightness/Pressure [see Warnings and Precautions (5.3)].
- Cerebrovascular Events [see Warnings and Precautions (5.4)].
- Other Vasospasm Reactions [see Warnings and Precautions (5.5)].
- Medication Overuse Headache [see Warnings and Precautions (5.6)].
- Serotonin Syndrome [see Warnings and Precautions (5.7)].
- Increase in Blood Pressure [see Warnings and Precautions (5.8)].

6.1 Clinical Trials Experience

Because clinical studies are conducted under widely varying conditions, adverse reaction rates observed in the clinical studies of a drug cannot be directly compared to rates in the clinical studies of another drug and may not reflect the rates observed in practice.

Adults

Incidence in Controlled Clinical Trials

Adverse reactions to MAXALT were assessed in controlled clinical trials that included over 3700 adult patients who received single or multiple doses of MAXALT Tablets. The most common adverse reactions during treatment with MAXALT (≥5% in either treatment group and greater than placebo) were asthenia/fatigue, somnolence, pain/pressure sensation and dizziness. These adverse reactions appeared to be dose related.

Table 1 lists the adverse reactions (incidence ≥2% and greater than placebo) after a single dose of MAXALT in adults.

Table 1: Incidence (≥2% and Greater than Placebo) of Adverse Reactions After a Single Dose of MAXALT Tablets or Placebo in Adults
 | % of Patients
Adverse Reactions | MAXALT 5 mg (N=977) | MAXALT 10 mg (N=1167) | Placebo (N=627)
Atypical Sensations | 4 | 5 | 4
Paresthesia | 3 | 4 | <2
Pain and other Pressure Sensations | 6 | 9 | 3
Chest Pain:
tightness/pressure and/or heaviness | <2 | 3 | 1
Neck/throat/jaw:
pain/tightness/pressure | <2 | 2 | 1
Regional Pain:
tightness/pressure and/or heaviness | <1 | 2 | 0
Pain, location unspecified | 3 | 3 | <2
Digestive | 9 | 13 | 8
Dry Mouth | 3 | 3 | 1
Nausea | 4 | 6 | 4
Neurological | 14 | 20 | 11
Dizziness | 4 | 9 | 5
Headache | <2 | 2 | <1
Somnolence | 4 | 8 | 4
Other
Asthenia/fatigue | 4 | 7 | 2

The frequencies of adverse reactions in clinical trials did not increase when up to three doses were taken within 24 hours. Adverse reaction frequencies were also unchanged by concomitant use of drugs commonly taken for migraine prophylaxis (including propranolol), oral contraceptives, or analgesics. The incidences of adverse reactions were not affected by age or gender. There were insufficient data to assess the impact of race on the incidence of adverse reactions.

Other Events Observed in Association with the Administration of MAXALT in Adults

In the following section, the frequencies of less commonly reported adverse events are presented that were not reported in other sections of the labeling. Because the reports include events observed in open studies, the role of MAXALT in their causation cannot be reliably determined. Furthermore, variability associated with adverse event reporting, the terminology used to describe adverse events, limit the value of the quantitative frequency estimates provided. Event frequencies are calculated as the number of patients who used MAXALT and reported an event divided by the total number of patients exposed to MAXALT (N=3716). All reported events occurred at an incidence ≥1%, or are believed to be reasonably associated with the use of the drug. Events are further classified within body system categories and enumerated in order of decreasing frequency using the following definitions: frequent adverse events are those defined as those occurring in at least (>)1/100 patients; infrequent adverse experiences are those occurring in 1/100 to 1/1000 patients; and rare adverse experiences are those occurring in fewer than 1/1000 patients.

General: Infrequent was facial edema. Rare were syncope and edema/swelling.

Atypical Sensations: Frequent were warm sensations.

Cardiovascular: Frequent was palpitation. Infrequent were tachycardia, cold extremities, and bradycardia.

Digestive: Frequent were diarrhea and vomiting. Infrequent were dyspepsia, tongue edema and abdominal distention.

Musculoskeletal: Infrequent were muscle weakness, stiffness, myalgia and muscle cramp/spasm.

Neurological/Psychiatric: Frequent were hypoesthesia, euphoria and tremor. Infrequent were vertigo, insomnia, confusion/disorientation, gait abnormality, memory impairment, and agitation.

Respiratory: Frequent was dyspnea. Infrequent was pharyngeal edema.

Special Senses: Infrequent were blurred vision and tinnitus. Rare was eye swelling.

Skin and Skin Appendage: Frequent was flushing. Infrequent were sweating, pruritus, rash, and urticaria. Rare was erythema, hot flashes.

The adverse reaction profile seen with MAXALT-MLT Orally Disintegrating Tablets was similar to that seen with MAXALT Tablets.

Pediatric Patients 6 to 17 Years of Age

Incidence in Controlled Clinical Trials in Pediatric Patients

Adverse reactions to MAXALT-MLT were assessed in a controlled clinical trial in the acute treatment of migraines (Study 7) that included a total of 1382 pediatric patients 6-17 years of age, of which 977 (72%) administered at least one dose of study treatment (MAXALT-MLT and/or placebo) [see Clinical Studies (14.2)]. The incidence of adverse reactions reported for pediatric patients in the acute clinical trial was similar in patients who received MAXALT to those who received placebo. The adverse reaction pattern in pediatric patients is expected to be similar to that in adults.

Other Events Observed in Association with the Administration of MAXALT-MLT in Pediatric Patients

In the following section, the frequencies of less commonly reported adverse events are presented. Because the reports include events observed in open studies, the role of MAXALT-MLT in their causation cannot be reliably determined. Furthermore, variability associated with adverse event reporting, the terminology used to describe adverse events, limit the value of the quantitative frequency estimates provided.

Event frequencies are calculated as the number of pediatric patients 6 to 17 years of age who used MAXALT-MLT and reported an event divided by the total number of patients exposed to MAXALT-MLT (N=1068). All reported events occurred at an incidence ≥1%, or are believed to be reasonably associated with the use of the drug. Events are further classified within system organ class and enumerated in order of decreasing frequency using the following definitions: frequent adverse events are those occurring in (>)1/100 pediatric patients; infrequent adverse experiences are those occurring in 1/100 to 1/1000 pediatric patients; and rare adverse experiences are those occurring in fewer than 1/1000 patients.

General: Frequent was fatigue.

Ear and labyrinth disorders: Infrequent was hypoacusis.

Gastrointestinal disorders: Frequent was abdominal discomfort.

Nervous system disorders: Infrequent were coordination abnormal, disturbance in attention, and presyncope.

Psychiatric disorders: Infrequent was hallucination.

6.2 Postmarketing Experience

The following section enumerates potentially important adverse events that have occurred in clinical practice and which have been reported spontaneously to various surveillance systems. The events enumerated include all except those already listed in other sections of the labeling or those too general to be informative. Because the reports cite events reported spontaneously from worldwide postmarketing experience, frequency of events and the role of MAXALT in their causation cannot be reliably determined.

Neurological/Psychiatric: Seizure.

General: Allergic conditions including anaphylaxis/anaphylactoid reaction, angioedema, wheezing, and toxic epidermal necrolysis [see Contraindications (4)].

Special Senses: Dysgeusia.

7 DRUG INTERACTIONS

7.1 Propranolol

The dose of MAXALT should be adjusted in propranolol-treated patients, as propranolol has been shown to increase the plasma AUC of rizatriptan by 70% [see Dosage and Administration (2.4) and Clinical Pharmacology (12.3)].

7.2 Ergot-Containing Drugs

Ergot-containing drugs have been reported to cause prolonged vasospastic reactions. Because these effects may be additive, use of ergotamine-containing or ergot-type medications (like dihydroergotamine or methysergide) and MAXALT within 24 hours is contraindicated [see Contraindications (4)].

7.3 Other 5-HT1 Agonists

Because their vasospastic effects may be additive, co-administration of MAXALT and other 5-HT1 agonists within 24 hours of each other is contraindicated [see Contraindications (4)].

7.4 SSRIs/SNRIs and Serotonin Syndrome

Cases of serotonin syndrome have been reported during co-administration of triptans and selective serotonin reuptake inhibitors (SSRIs) or serotonin norepinephrine reuptake inhibitors (SNRIs) [see Warnings and Precautions (5.7)].

7.5 Monoamine Oxidase Inhibitors

MAXALT is contraindicated in patients taking MAO-A inhibitors and non-selective MAO inhibitors. A specific MAO-A inhibitor increased the systemic exposure of rizatriptan and its metabolite [see Contraindications (4) and Clinical Pharmacology (12.3)].

8 USE IN SPECIFIC POPULATIONS

8.1 Pregnancy

Risk Summary

Available human data on the use of MAXALT in pregnant women are not sufficient to draw conclusions about drug-associated risk for major birth defects and miscarriage.

In animal studies, developmental toxicity was observed following oral administration of rizatriptan during pregnancy (decreased fetal body weight in rats) or throughout pregnancy and lactation (increased mortality, decreased body weight, and neurobehavioral impairment in rat offspring) at maternal plasma exposures greater than that expected at therapeutic doses in humans [see Animal Data].

In the U.S. general population, the estimated background risk of major birth defects and of miscarriage in clinically recognized pregnancies is 2% to 4% and 15% to 20%, respectively. The reported rate of major birth defects among deliveries to women with migraine range from 2.2% to 2.9% and the reported rate of miscarriage was 17%, which are similar to rates reported in women without migraine.

Clinical Considerations

Disease-Associated Maternal and/or Embryo/Fetal Risk

In women with migraine, there is an increased risk of adverse perinatal outcomes in the mother, including pre-eclampsia and gestational hypertension.

Data

Human Data

The Pregnancy Registry for MAXALT did not identify any pattern of congenital anomalies or other adverse birth outcomes over the period of 1998 to 2018. However, the lack of identification of any pattern should be viewed with caution, as the number of prospective reports with outcome information was low and did not provide sufficient power to detect an increased risk of individual birth defects associated with the use of MAXALT. Additionally, there was significant loss to follow-up in the prospective pregnancy reports, further complicating this assessment of an association between MAXALT and any pattern of congenital anomalies or other adverse birth outcomes.

In a study using data from the Swedish Medical Birth Register, live births to women who reported using triptans or ergots during pregnancy were compared with those of women who did not. Of the 157 births with first-trimester exposure to rizatriptan, 7 infants were born with malformations (relative risk 1.01 [95% CI: 0.40 to 2.08]). A study using linked data from the Medical Birth Registry of Norway to the Norwegian Prescription Database compared pregnancy outcomes in women who redeemed prescriptions for triptans during pregnancy, as well as a migraine disease comparison group who redeemed prescriptions for triptans before pregnancy only, compared with a population control group. Of the 310 women who redeemed prescriptions for rizatriptan during the first trimester, 10 had infants with major congenital malformations (OR 1.03 [95% CI: 0.55 to 1.93]), while for the 271 women who redeemed prescriptions for rizatriptan before, but not during, pregnancy, 12 had infants with major congenital malformations (OR 1.48 [95% CI: 0.83 to 2.64]), each compared with the population comparison group.

Animal Data

When rizatriptan (0, 2, 10, or 100 mg/kg/day) was administered orally to pregnant rats throughout organogenesis, a decrease in fetal body weight was observed at the highest doses tested. At the mid dose (10 mg/kg/day), which was a no-effect dose for adverse effects on embryofetal development, plasma exposure (AUC) was approximately 15 times that in humans at the maximum recommended human dose (MRHD) of 30 mg/day. When rizatriptan (0, 5, 10, or 50 mg/kg/day) was administered orally to pregnant rabbits throughout organogenesis, no adverse fetal effects were observed. Plasma exposure (AUC) at the highest dose tested was 115 times that in humans at the MRHD. Placental transfer of drug to the fetus was demonstrated in both species.

Oral administration of rizatriptan (0, 2, 10, or 100 mg/kg/day) to female rats prior to and during mating and continuing throughout gestation and lactation resulted in reduced body weight in offspring from birth and throughout lactation at all but the lowest dose tested (2 mg/kg/day). Plasma exposure (AUC) at the no-effect dose (2 mg/kg/day) for adverse effects on postnatal development was similar to that in humans at the MRHD.

Oral administration of rizatriptan (0, 5, 100, or 250 mg/kg/day) throughout organogenesis and lactation resulted in neonatal mortality, reduced body weight (which persisted into adulthood), and impaired neurobehavioral function in offspring at all but the lowest dose tested. Plasma exposure (AUC) at the no-effect dose for adverse effects on postnatal development (5 mg/kg/day) was approximately 8 times that in humans at the MRHD.

8.2 Lactation

Risk Summary

There are no data on the presence of rizatriptan or any active metabolites in human milk, or on the effects of rizatriptan on the breastfed infant, or on milk production.

Rizatriptan was excreted in rat milk, with levels in milk approximately 6 times those in maternal plasma.

The developmental and health benefits of breastfeeding should be considered along with the mother's clinical need for MAXALT or MAXALT-MLT and any potential adverse effects on the breastfed infant from MAXALT or MAXALT-MLT or from the underlying maternal condition.

Data

Following oral administration of rizatriptan to lactating rats at a dose of 100 mg/kg/day, drug concentrations of rizatriptan in milk samples exceeded maternal plasma drug concentrations by approximately 6-fold.

8.4 Pediatric Use

Safety and effectiveness in pediatric patients under 6 years of age have not been established.

The efficacy and safety of MAXALT in the acute treatment of migraine in patients aged 6 to 17 years was established in an adequate and well-controlled study [see Clinical Studies (14.2)].

The incidence of adverse reactions reported for pediatric patients in the acute clinical trial was similar in patients who received MAXALT to those who received placebo. The adverse reaction pattern in pediatric patients is expected to be similar to that in adults.

8.5 Geriatric Use

Clinical studies of MAXALT did not include sufficient numbers of subjects aged 65 and over to determine whether they respond differently from younger subjects. Other reported clinical experience has not identified differences in responses between the elderly and younger patients.

Although the pharmacokinetics of rizatriptan were similar in elderly (aged ≥65 years) and in younger adults (n=17), in general, dose selection for an elderly patient should be cautious, starting at the low end of the dosing range. This reflects the greater frequency of decreased hepatic, renal, or cardiac function, and of concomitant disease or other drug therapy.

Geriatric patients who have other cardiovascular risk factors (e.g., diabetes, hypertension, smoking, obesity, strong family history of coronary artery disease) should have a cardiovascular evaluation prior to receiving MAXALT [see Warnings and Precautions (5.1)].

8.6 Patients with Phenylketonuria

Orally Disintegrating Tablets contain phenylalanine (a component of aspartame). The 10-mg orally disintegrating tablets contain 2.1 mg phenylalanine.

10 OVERDOSAGE

No overdoses of MAXALT were reported during clinical trials in adults.

Some adult patients who received 40 mg of MAXALT either a single dose or as two doses with a 2-hour interdose interval had dizziness and somnolence.

In a clinical pharmacology study in which 12 adult subjects received MAXALT, at total cumulative doses of 80 mg (given within four hours), two of the subjects experienced syncope, dizziness, bradycardia including third degree AV block, vomiting, and/or incontinence.

In the long-term, open label study, involving 606 treated pediatric migraineurs 12 to 17 years of age (of which 432 were treated for at least 12 months), 151 patients (25%) took two 10-mg doses of MAXALT-MLT within a 24-hour period. Adverse reactions for 3 of these patients included abdominal discomfort, fatigue, and dyspnea.

In addition, based on the pharmacology of MAXALT, hypertension or myocardial ischemia could occur after overdosage. Gastrointestinal decontamination, (i.e., gastric lavage followed by activated charcoal) should be considered in patients suspected of an overdose with MAXALT. Clinical and electrocardiographic monitoring should be continued for at least 12 hours, even if clinical symptoms are not observed.

The effects of hemo- or peritoneal dialysis on serum concentrations of rizatriptan are unknown.

11 DESCRIPTION

MAXALT contains rizatriptan benzoate, a selective 5-hydroxytryptamine1B/1D (5-HT1B/1D) receptor agonist.

Rizatriptan benzoate is described chemically as: N,N-dimethyl-5-(1H-1,2,4-triazol-1-ylmethyl)-1H-indole-3-ethanamine monobenzoate and its structural formula is:

Its empirical formula is C15H19N5•C7H6O2, representing a molecular weight of the free base of 269.4. Rizatriptan benzoate is a white to off-white, crystalline solid that is soluble in water at about 42 mg per mL (expressed as free base) at 25°C.

MAXALT Tablets and MAXALT-MLT Orally Disintegrating Tablets are available for oral administration in a strength of 10 mg (corresponding to 14.53 mg of the benzoate salt). Each compressed tablet contains the following inactive ingredients: lactose monohydrate, microcrystalline cellulose, pregelatinized starch, ferric oxide (red), and magnesium stearate.

Each lyophilized orally disintegrating tablet contains the following inactive ingredients: gelatin, mannitol, glycine, aspartame, and peppermint flavor.

12 CLINICAL PHARMACOLOGY

12.1 Mechanism of Action

Rizatriptan binds with high affinity to human cloned 5-HT1B/1D receptors. MAXALT presumably exerts its therapeutic effects in the treatment of migraine headache by binding to 5-HT1B/1D receptors located on intracranial blood vessels and sensory nerves of the trigeminal system.

12.3 Pharmacokinetics

Absorption

Rizatriptan is completely absorbed following oral administration. The mean oral absolute bioavailability of the MAXALT Tablet is about 45%, and mean peak plasma concentrations (Cmax) are reached in approximately 1-1.5 hours (Tmax). The presence of a migraine headache did not appear to affect the absorption or pharmacokinetics of rizatriptan. Food has no significant effect on the bioavailability of rizatriptan but delays the time to reach peak concentration by an hour. In clinical trials, MAXALT was administered without regard to food.

The bioavailability and Cmax of rizatriptan were similar following administration of MAXALT Tablets and MAXALT-MLT Orally Disintegrating Tablets, but the rate of absorption is somewhat slower with MAXALT-MLT, with Tmax delayed by up to 0.7 hour. AUC of rizatriptan is approximately 30% higher in females than in males. No accumulation occurred on multiple dosing.

Distribution

The mean volume of distribution is approximately 140 liters in male subjects and 110 liters in female subjects. Rizatriptan is minimally bound (14%) to plasma proteins.

Metabolism

The primary route of rizatriptan metabolism is via oxidative deamination by monoamine oxidase-A (MAO-A) to the indole acetic acid metabolite, which is not active at the 5-HT1B/1D receptor. N-monodesmethyl-rizatriptan, a metabolite with activity similar to that of parent compound at the 5-HT1B/1D receptor, is formed to a minor degree. Plasma concentrations of N-monodesmethyl-rizatriptan are approximately 14% of those of parent compound, and it is eliminated at a similar rate. Other minor metabolites, the N-oxide, the 6-hydroxy compound, and the sulfate conjugate of the 6-hydroxy metabolite are not active at the 5-HT1B/1D receptor.

Elimination

The total radioactivity of the administered dose recovered over 120 hours in urine and feces was 82% and 12%, respectively, following a single 10-mg oral administration of ^14C-rizatriptan. Following oral administration of ^14C-rizatriptan, rizatriptan accounted for about 17% of circulating plasma radioactivity. Approximately 14% of an oral dose is excreted in urine as unchanged rizatriptan while 51% is excreted as indole acetic acid metabolite, indicating substantial first pass metabolism.

The plasma half-life of rizatriptan in males and females averages 2-3 hours.

Cytochrome P450 Isoforms

Rizatriptan is not an inhibitor of the activities of human liver cytochrome P450 isoforms 3A4/5, 1A2, 2C9, 2C19, or 2E1; rizatriptan is a competitive inhibitor (Ki=1400 nM) of cytochrome P450 2D6, but only at high, clinically irrelevant concentrations.

Special Populations

Geriatric: Rizatriptan pharmacokinetics in healthy elderly non-migraineur volunteers (age 65-77 years) were similar to those in younger non-migraineur volunteers (age 18-45 years).

Pediatric: The pharmacokinetics of rizatriptan was determined in pediatric migraineurs 6 to 17 years of age. Exposures following single dose administration of 5 mg MAXALT-MLT to pediatric patients weighing 20-39 kg (44-87 lb) or 10 mg MAXALT-MLT to pediatric patients weighing ≥40 kg (88 lb) were similar to those observed following single dose administration of 10 mg MAXALT-MLT to adults.

Gender: The mean AUC0-∞ and Cmax of rizatriptan (10 mg orally) were about 30% and 11% higher in females as compared to males, respectively, while Tmax occurred at approximately the same time.

Hepatic impairment: Following oral administration in patients with hepatic impairment caused by mild to moderate alcoholic cirrhosis of the liver, plasma concentrations of rizatriptan were similar in patients with mild hepatic insufficiency compared to a control group of subjects with normal hepatic function; plasma concentrations of rizatriptan were approximately 30% greater in patients with moderate hepatic insufficiency.

Renal impairment: In patients with renal impairment (creatinine clearance 10-60 mL/min/1.73 m^2), the AUC0-∞ of rizatriptan was not significantly different from that in subjects with normal renal function. In hemodialysis patients, (creatinine clearance <2 mL/min/1.73 m^2), however, the AUC for rizatriptan was approximately 44% greater than that in patients with normal renal function.

Race: Pharmacokinetic data revealed no significant differences between African American and Caucasian subjects.

Drug Interactions

[See also Drug Interactions (7).]

Monoamine oxidase inhibitors: Rizatriptan is principally metabolized via monoamine oxidase, 'A' subtype (MAO-A). Plasma concentrations of rizatriptan may be increased by drugs that are selective MAO-A inhibitors (e.g., moclobemide) or nonselective MAO inhibitors [type A and B] (e.g., isocarboxazid, phenelzine, tranylcypromine, and pargyline). In a drug interaction study, when MAXALT 10 mg was administered to subjects (n=12) receiving concomitant therapy with the selective, reversible MAO-A inhibitor, moclobemide 150 mg t.i.d., there were mean increases in rizatriptan AUC and Cmax of 119% and 41% respectively; and the AUC of the active N-monodesmethyl metabolite of rizatriptan was increased more than 400%. The interaction would be expected to be greater with irreversible MAO inhibitors. No pharmacokinetic interaction is anticipated in patients receiving selective MAO-B inhibitors [see Contraindications (4) and Drug Interactions (7.5)].

Propranolol: In a study of concurrent administration of propranolol 240 mg/day and a single dose of rizatriptan 10 mg in healthy adult subjects (n=11), mean plasma AUC for rizatriptan was increased by 70% during propranolol administration, and a four-fold increase was observed in one subject. The AUC of the active N-monodesmethyl metabolite of rizatriptan was not affected by propranolol [see Dosage and Administration (2.4) and Drug Interactions (7.1)].

Nadolol/Metoprolol: In a drug interactions study, effects of multiple doses of nadolol 80 mg or metoprolol 100 mg every 12 hours on the pharmacokinetics of a single dose of 10 mg rizatriptan were evaluated in healthy subjects (n=12). No pharmacokinetic interactions were observed.

Paroxetine: In a study of the interaction between the selective serotonin reuptake inhibitor (SSRI) paroxetine 20 mg/day for two weeks and a single dose of MAXALT 10 mg in healthy subjects (n=12), neither the plasma concentrations of rizatriptan nor its safety profile were affected by paroxetine [see Warnings and Precautions (5.7), Drug Interactions (7.4), and Patient Counseling Information (17)].

Oral contraceptives: In a study of concurrent administration of an oral contraceptive during 6 days of administration of MAXALT (10-30 mg/day) in healthy female volunteers (n=18), rizatriptan did not affect plasma concentrations of ethinyl estradiol or norethindrone.

13 NONCLINICAL TOXICOLOGY

13.1 Carcinogenesis, Mutagenesis, Impairment of Fertility

Carcinogenesis

Oral carcinogenicity studies of rizatriptan were conducted in mice (100 weeks) and rats (106 weeks) at doses of up to 125 mg/kg/day. There was no evidence of an increase in tumor incidence related to rizatriptan in either species. Plasma exposures (AUC) at the highest dose tested were approximately 150 (mice) and 240 times (rats) that in humans at the maximum recommended human dose (MRHD) of 30 mg/day.

Mutagenesis

Rizatriptan was neither mutagenic nor clastogenic in a battery of in vitro and in vivo genetic toxicity studies, including: the microbial mutagenesis (Ames) assay, in vitro mammalian cell mutagenesis and chromosomal aberration assays, and the in vivo chromosomal aberration assay in mouse.

Impairment of Fertility

Oral administration of rizatriptan (0, 2, 10, or 100 mg/kg/day) to female rats prior to and during mating and continuing throughout gestation and lactation resulted in no effect on fertility; however, altered estrous cyclicity and delays in time to mating were observed at the highest dose tested. Plasma exposure at the no-effect dose (10 mg/kg/day) for reproductive toxicity was approximately 15 times that in humans at the MRHD.

Oral administration of rizatriptan (0, 5, 35, or 250 mg/kg/day) to male rats prior to and during mating resulted in no impairment of fertility or reproductive performance. Plasma exposure (AUC) at the highest dose tested was approximately 550 times that in humans at the MRHD.

14 CLINICAL STUDIES

14.1 Adults

The efficacy of MAXALT Tablets was established in four multicenter, randomized, placebo-controlled trials. Patients enrolled in these studies were primarily female (84%) and Caucasian (88%), with a mean age of 40 years (range of 18 to 71). Patients were instructed to treat a moderate to severe headache. Headache response, defined as a reduction of moderate or severe headache pain to no or mild headache pain, was assessed for up to 2 hours (Study 1) or up to 4 hours after dosing (Studies 2, 3 and 4). Associated symptoms of nausea, photophobia, and phonophobia and maintenance of response up to 24 hours post-dose were evaluated. A second dose of MAXALT Tablets was allowed 2 to 24 hours after dosing for treatment of recurrent headache in Studies 1 and 2. Additional analgesics and/or antiemetics were allowed 2 hours after initial treatment for rescue in all four studies.

In all studies, the percentage of patients achieving headache response 2 hours after treatment was significantly greater in patients who received either MAXALT 5 or 10 mg compared to those who received placebo. In a separate study, doses of 2.5 mg were not different from placebo. Doses greater than 10 mg were associated with an increased incidence of adverse effects. The results from the four controlled studies are summarized in Table 2.

Table 2: Response Rates 2 Hours Following Treatment of Initial Headache in Studies 1, 2, 3, and 4
Study | Placebo | MAXALT Tablets 5 mg | MAXALT Tablets 10 mg
1 | 35% (n=304) | 62% [p-value <0.05 in comparison with placebo.] (n=458) | 71%, [p-value <0.05 in comparison with 5 mg.] (n=456)
2 [Results for initial headache only.] | 37% (n=82) | — | 77% (n=320)
3 | 23% (n=80) | 63% (n=352) | —
4 | 40% (n=159) | 60% (n=164) | 67% (n=385)

Comparisons of drug performance based upon results obtained in different clinical trials may not be reliable. Because studies are conducted at different times, with different samples of patients, by different investigators, employing different criteria and/or different interpretations of the same criteria, under different conditions (dose, dosing regimen, etc.), quantitative estimates of treatment response and the timing of response may be expected to vary considerably from study to study.

The estimated probability of achieving an initial headache response within 2 hours following treatment in pooled Studies 1, 2, 3, and 4 is depicted in Figure 1.

Figure 1: Estimated Probability of Achieving an Initial Headache Response by 2 Hours in Pooled Studies 1, 2, 3, and 4 [Figure 1 shows the Kaplan-Meier plot of the probability over time of obtaining headache response (no or mild pain) following treatment with MAXALT or placebo. The averages displayed are based on pooled data from 4 placebo-controlled, outpatient trials providing evidence of efficacy (Studies 1, 2, 3, and 4). Patients taking additional treatment or not achieving headache response prior to 2 hours were censored at 2 hours.]

For patients with migraine-associated photophobia, phonophobia, and nausea at baseline, there was a decreased incidence of these symptoms following administration of MAXALT compared to placebo.

Two to 24 hours following the initial dose of study treatment, patients were allowed to use additional treatment for pain response in the form of a second dose of study treatment or other medication. The estimated probability of patients taking a second dose or other medication for migraine over the 24 hours following the initial dose of study treatment is summarized in Figure 2.

Figure 2: Estimated Probability of Patients Taking a Second Dose of MAXALT Tablets or Other Medication for Migraines Over the 24 Hours Following the Initial Dose of Study Treatment in Pooled Studies 1, 2, 3, and 4 [This Kaplan-Meier plot is based on data obtained in 4 placebo-controlled outpatient clinical trials (Studies 1, 2, 3, and 4). Patients not using additional treatments were censored at 24 hours. The plot includes both patients who had headache response at 2 hours and those who had no response to the initial dose. Remedication was not allowed within 2 hours post-dose.]

Efficacy was unaffected by the presence of aura; by the gender, or age of the patient; or by concomitant use of common migraine prophylactic drugs (e.g., beta-blockers, calcium channel blockers, tricyclic antidepressants) or oral contraceptives. In two additional similar studies, efficacy was unaffected by relationship to menses. There were insufficient data to assess the impact of race on efficacy.

MAXALT-MLT Orally Disintegrating Tablets

The efficacy of MAXALT-MLT was established in two multicenter, randomized, placebo-controlled trials that were similar in design to the trials of MAXALT Tablets (Studies 5 and 6). Patients were instructed to treat a moderate to severe headache. Patients treated in these studies were primarily female (88%) and Caucasian (95%), with a mean age of 42 years (range 18-72).

In both studies, the percentage of patients achieving headache response 2 hours after treatment was significantly greater in patients who received either MAXALT-MLT 5 or 10 mg compared to those who received placebo. The results from Studies 5 and 6 are summarized in Table 3.

Table 3: Response Rates 2 Hours Following Treatment of Initial Headache in Studies 5 and 6
Study | Placebo | MAXALT-MLT 5 mg | MAXALT-MLT 10 mg
5 | 47% (n=98) | 66% [p-value <0.01 in comparison with placebo.] (n=100) | 66% (n=113)
6 | 28% (n=180) | 59% (n=181) | 74%, [p-value <0.01 in comparison with 5 mg.] (n=186)

The estimated probability of achieving an initial headache response by 2 hours following treatment with MAXALT-MLT in pooled Studies 5 and 6 is depicted in Figure 3.

Figure 3: Estimated Probability of Achieving an Initial Headache Response with MAXALT-MLT by 2 Hours in Pooled Studies 5 and 6 [Figure 3 shows the Kaplan-Meier plot of the probability over time of obtaining headache response (no or mild pain) following treatment with MAXALT-MLT or placebo. The averages displayed are based on pooled data from 2 placebo-controlled, outpatient trials providing evidence of efficacy (Studies 5 and 6). Patients taking additional treatment or not achieving headache response prior to 2 hours were censored at 2 hours.]

For patients with migraine-associated photophobia and phonophobia at baseline, there was a decreased incidence of these symptoms following administration of MAXALT-MLT as compared to placebo.

Two to 24 hours following the initial dose of study treatment, patients were allowed to use additional treatment for pain response in the form of a second dose of study treatment or other medication. The estimated probability of patients taking a second dose or other medication for migraine over the 24 hours following the initial dose of study treatment is summarized in Figure 4.

Figure 4: Estimated Probability of Patients Taking a Second Dose of MAXALT-MLT or Other Medication for Migraines Over the 24 Hours Following the Initial Dose of Study Treatment in Pooled Studies 5 and 6 [This Kaplan-Meier plot is based on data obtained in 2 placebo-controlled outpatient clinical trials (Studies 5 and 6). Patients not using additional treatments were censored at 24 hours. The plot includes both patients who had headache response at 2 hours and those who had no response to the initial dose. Remedication was not allowed within 2 hours post-dose.]

14.2 Pediatric Patients 6 to 17 Years of Age

The efficacy of MAXALT-MLT in pediatric patients 6 to 17 years was evaluated in a multicenter, randomized, double-blind, placebo-controlled, parallel group clinical trial (Study 7). Patients had to have at least a 6-month history of migraine attacks (with or without aura) usually lasting 3 hours or more (when untreated). The patient population was historically non-responsive to NSAIDs and acetaminophen therapy.

Patients were instructed to treat a single migraine attack with headache pain of moderate to severe intensity. The treatment phase of the study had two stages. Stage 1 was used to identify placebo non-responders, who then entered into Stage 2, in which patients were randomized to MAXALT-MLT or placebo. Using a weight-based dosing strategy, patients 20 kg to <40 kg (44 lb to <88 lb) received MAXALT-MLT 5 mg or placebo, and patients ≥40 kg (88 lb) received MAXALT-MLT 10 mg or placebo.

The mean age for the studied patient population was 13 years. Sixty-one percent of the patients were Caucasian, and fifty-six percent of the patients were female. The percentage of patients achieving the primary efficacy endpoint of no headache pain at 2 hours after treatment was significantly greater in patients who received MAXALT-MLT, compared with those who received placebo (33% vs. 24%). Study 7 results are summarized in Table 4.

Table 4: Response Rates 2 Hours Following Treatment of Initial Headache in Pediatric Patients 6 to 17 Years of Age in Study 7
Endpoint | Placebo | MAXALT-MLT | p-Value
No headache pain at 2 hours post-dose | 24% (n/m=94/388) | 33% (n/m=126/382) | 0.01
n = Number of evaluable patients with no headache pain at 2 hours post-dose.
m = Number of evaluable patients in population.

The observed percentage of pediatric patients achieving no headache pain within 2 hours following initial treatment with MAXALT-MLT is shown in Figure 5.

Figure 5: Observed Percentage of Patients Reporting No Headache Pain by 2 Hours Post-Dose in Study 7

The prevalence of the exploratory endpoints of absence of migraine-associated symptoms (nausea, photophobia, and phonophobia) at 2 hours after taking the dose was not statistically significantly different between patients who received MAXALT-MLT and those who received placebo.

16 HOW SUPPLIED/STORAGE AND HANDLING

MAXALT Tablets, 10 mg, are pale pink, capsule-shaped, compressed tablets coded MAXALT on one side and MRK 267 on the other:

NDC 78206-142-01, carton of 18 tablets.

MAXALT-MLT Orally Disintegrating Tablets, 10 mg, are white to off-white, round lyophilized orally disintegrating tablets debossed with a modified square on one side, and measuring 12.0-13.8 mm (side-to-side) with a peppermint flavor. Each orally disintegrating tablet is individually packaged in a blister inside an aluminum pouch (sachet). They are supplied as follows:

NDC 78206-143-01, 6 × unit of use carrying case of 3 orally disintegrating tablets (18 tablets total).

Storage

Store MAXALT Tablets at room temperature, 15°C-30°C (59°F-86°F).

Store MAXALT-MLT Orally Disintegrating Tablets at room temperature, 15°C-30°C (59°F-86°F).

17 PATIENT COUNSELING INFORMATION

Advise the patient to read the FDA-approved patient labeling (Patient Information).

Risk of Myocardial Ischemia and/or Infarction, Prinzmetal's Angina, Other Vasospasm-Related Events, and Cerebrovascular Events

Inform patients that MAXALT may cause serious cardiovascular side effects such as myocardial infarction or stroke. Although serious cardiovascular events can occur without warning symptoms, patients should be alert for the signs and symptoms of chest pain, shortness of breath, weakness, slurring of speech, and should ask for medical advice when observing any indicative sign or symptoms. Patients should be apprised of the importance of this follow-up [see Warnings and Precautions (5.1, 5.2, 5.4, 5.5)].

Serotonin Syndrome

Patients should be cautioned about the risk of serotonin syndrome with the use of MAXALT or other triptans, particularly during combined use with selective serotonin reuptake inhibitors (SSRIs) or serotonin norepinephrine reuptake inhibitors (SNRIs) [see Warnings and Precautions (5.7), Drug Interactions (7.4), and Clinical Pharmacology (12.3)].

Pregnancy

Inform patients that MAXALT should not be used during pregnancy unless the potential benefit justifies the potential risk to the fetus [see Use in Specific Populations (8.1)].

Lactation

Advise patients to notify their healthcare provider if they are breastfeeding or plan to breastfeed [see Use in Specific Populations (8.2)].

Ability to Perform Complex Tasks

Since migraines or treatment with MAXALT may cause somnolence and dizziness, instruct patients to evaluate their ability to perform complex tasks during migraine attacks and after administration of MAXALT.

Medication Overuse Headache

Inform patients that use of acute migraine drugs for 10 or more days per month may lead to an exacerbation of headache, and encourage patients to record headache frequency and drug use (e.g., by keeping a headache diary) [see Warnings and Precautions (5.6)].

Handling of Orally Disintegrating Tablets Packages

Instruct patients not to remove the blister from the outer aluminum pouch until ready to use the orally disintegrating tablet inside [see Dosage and Administration (2.3)].

Patients with Phenylketonuria

Inform phenylketonuric patients that MAXALT-MLT Orally Disintegrating Tablets contain phenylalanine (a component of aspartame). Each 10-mg orally disintegrating tablet contains 2.1 mg phenylalanine [see Use in Specific Populations (8.6)].

MAXALT Tablets and MAXALT-MLT Orally Disintegrating Tablets are distributed by:
Organon LLC, a subsidiary of
ORGANON & Co.,
Jersey City, NJ 07302, USA

For patent information: www.organon.com/our-solutions/patent/

Copyright © 2021 Organon Global Inc.
All rights reserved.

uspi-og0462-t-tol-2106r000

Patient Information
MAXALT® (max-awlt) and MAXALT-MLT®
rizatriptan benzoate
Tablets and Orally Disintegrating Tablets

Read this Patient Information before you start taking MAXALT® and each time you get a refill. There may be new information. This information does not take the place of talking to your doctor about your medical condition or your treatment.

Unless otherwise stated, the information in this Patient Information leaflet applies to both MAXALT Tablets and to MAXALT-MLT® Orally Disintegrating Tablets.

What is MAXALT?

MAXALT is a prescription medicine that belongs to a class of medicines called Triptans. MAXALT is available as a traditional tablet (MAXALT) and as an orally disintegrating tablet (MAXALT-MLT).

MAXALT and MAXALT-MLT are used to treat migraine attacks with or without aura in adults and in children 6 to 17 years of age.

MAXALT is not to be used to prevent migraine attacks.

MAXALT is not for the treatment of hemiplegic or basilar migraines.

It is not known if MAXALT is safe and effective for the treatment of cluster headaches.

It is not known if taking more than 1 dose of MAXALT in 24 hours is safe and effective in children 6 to 17 years of age.

It is not known if MAXALT is safe and effective in children under 6 years of age.

Who should not take MAXALT?

Do not take MAXALT if you:

- have or have had heart problems
- have or have had a stroke or a transient ischemic attack (TIA)
- have or have had blood vessel problems including ischemic bowel disease
- have uncontrolled high blood pressure
- have taken other Triptan medicines in the last 24 hours
- have taken ergot-containing medicines in the last 24 hours
- have hemiplegic or basilar migraines
- take monoamine oxidase (MAO) inhibitor or have taken a MAO inhibitor within the last 2 weeks
- are allergic to rizatriptan benzoate or any of the ingredients in MAXALT. See the end of this leaflet for a complete list of ingredients in MAXALT.

Talk to your doctor before taking this medicine if you have any of the conditions listed above or if you are not sure if you take any of these medicines.

What should I tell my doctor before taking MAXALT?

Before you take MAXALT, tell your doctor if you:

- have or have had heart problems, high blood pressure, chest pain, or shortness of breath
- have any risk factors for heart problems or blood vessel problems such as:
  - high blood pressure
  - high cholesterol
  - smoking
  - obesity
  - diabetes
  - family history of heart problems
  - you are post menopausal
  - you are a male over 40
- have phenylketonuria (PKU). MAXALT-MLT orally disintegrating tablets contain phenylalanine.
- have kidney or liver problems
- have any other medical condition
- are pregnant or plan to become pregnant. It is not known if MAXALT will harm your unborn baby. If you become pregnant while taking MAXALT, talk to your healthcare provider.
- are breastfeeding or plan to breastfeed. It is not known if MAXALT passes into your breast milk. Talk to your doctor about the best way to feed your baby if you take MAXALT.

Tell your doctor about all the medicines you take, including prescription and nonprescription medicines, vitamins, and herbal supplements.

MAXALT and other medicines may affect each other causing side effects. MAXALT may affect the way other medicines work, and other medicines may affect how MAXALT works.

Especially tell your doctor if you take:

- propranolol containing medicines such as Inderal®, Inderal® LA, or Innopran® XL
- medicines used to treat mood disorders, including selective serotonin reuptake inhibitors (SSRIs) or serotonin norepinephrine reuptake inhibitors (SNRIs).

Ask your doctor or pharmacist for a list of these medicines, if you are not sure.

Know the medicines you take. Keep a list of them to show your doctor and pharmacist when you get a new medicine.

How should I take MAXALT?

- Take MAXALT exactly as your doctor tells you to take it.
- Your doctor will tell you how much MAXALT to take and when to take it.
- To take MAXALT-MLT:
  - Leave MAXALT-MLT orally disintegrating tablets in the package it comes in until you are ready to take it. When you are ready to take it:
    - Remove the blister from the foil pouch. Do not push the MAXALT-MLT orally disintegrating tablet through the blister.
    - Peel open the blister pack with dry hands and place the MAXALT-MLT orally disintegrating tablet on your tongue. The tablet will dissolve and be swallowed with your saliva. No liquid is needed to take the orally disintegrating tablet.
- If your headache comes back after your first MAXALT dose:
  - For adults: a second dose may be taken 2 hours after the first dose. Do not take more than 30 mg of MAXALT in a 24-hour period (for example, do not take more than 3 10-mg tablets in a 24-hour period).
  - For children 6 to 17 years of age: It is not known if taking more than 1 dose of MAXALT in 24 hours is safe and effective. Talk to your doctor about what to do if your headache does not go away or comes back.
- If you take too much MAXALT, call your doctor or go to the nearest hospital emergency room right away.

What should I avoid while taking MAXALT?

MAXALT may cause dizziness, weakness, or fainting. If you have these symptoms, do not drive a car, use machinery, or do anything that needs you to be alert.

What are the possible side effects of MAXALT?

MAXALT may cause serious side effects. Call your doctor or go to the nearest hospital emergency room right away if you think you are having any of the serious side effects of MAXALT including:

- heart attack. Symptoms of a heart attack may include:
  - chest discomfort in the center of your chest that lasts for more than a few minutes or that goes away and comes back
  - chest discomfort that feels like uncomfortable pressure, squeezing, fullness or pain
  - pain or discomfort in your arms, back, neck, jaw or stomach
  - shortness of breath with or without chest discomfort
  - breaking out in a cold sweat
  - nausea or vomiting
  - feeling lightheaded
- stroke. Symptoms of a stroke may include the following sudden symptoms:
  - numbness or weakness in your face, arm or leg, especially on one side of your body
  - confusion, problems speaking or understanding
  - problems seeing in 1 or both of your eyes
  - problems walking, dizziness, loss of balance or coordination
  - severe headache with no known cause
- blood vessel problems. Symptoms of blood vessel problems may include:
  - stomach pain
  - bloody diarrhea
  - vision problems
  - coldness and numbness of hands and feet
- serotonin syndrome. A condition called serotonin syndrome can happen when Triptan medicines such as MAXALT are taken with certain other medicines. Symptoms of serotonin syndrome may include:
  - agitation
  - hallucinations
  - coma
  - fast heartbeat
  - fast changes in your blood pressure
  - increased body temperature
  - muscle spasm
  - loss of coordination
  - nausea, vomiting or diarrhea
- increased blood pressure.

The most common side effects of MAXALT in adults include:

- feeling sleepy or tired
- pain or pressure in your chest or throat
- dizziness

Tell your doctor if you have any side effect that bothers you or that does not go away.

If you take MAXALT too often, this may result in you getting chronic headaches. In such cases, you should contact your doctor, as you may have to stop taking MAXALT.

These are not all the possible side effects of MAXALT. For more information, ask your doctor or pharmacist.

Call your doctor for medical advice about side effects. You may report side effects to FDA at 1-800-FDA-1088.

How should I store MAXALT?

- Store MAXALT at room temperature between 59°F to 86°F (15°C to 30°C).
- Safely throw away medicine that is out of date or no longer needed.

Keep MAXALT and all medicines out of the reach of children.

General Information about the safe and effective use of MAXALT.

Medicines are sometimes prescribed for purposes other than those listed in a Patient Information leaflet. Do not use MAXALT for a condition for which it was not prescribed. Do not give MAXALT to other people, even if they have the same symptoms that you have. It may harm them.

This Patient Information leaflet summarizes the most important information about MAXALT. If you would like more information, talk to your doctor. You can ask your pharmacist or doctor for information about MAXALT that is written for health professionals.

What are the ingredients in MAXALT?

Active ingredient in MAXALT and MAXALT-MLT orally disintegrating tablets:

rizatriptan benzoate.

Inactive ingredients in MAXALT: lactose monohydrate, microcrystalline cellulose, pregelatinized starch, ferric oxide (red), and magnesium stearate.

Inactive ingredients in MAXALT-MLT orally disintegrating tablets: gelatin, mannitol, glycine, aspartame, and peppermint flavor.

MAXALT-MLT orally disintegrating tablets contain aspartame, a source of phenylalanine.

Phenylketonurics:

MAXALT-MLT orally disintegrating tablets 10-mg contain 2.1 mg of phenylalanine.

This Patient Information has been approved by the U.S. Food and Drug Administration.

MAXALT Tablets and MAXALT-MLT Orally Disintegrating Tablets are distributed by:
Organon LLC, a subsidiary of
ORGANON & Co.,
Jersey City, NJ 07302, USA

For patent information: www.organon.com/our-solutions/patent/

The brands listed are the trademarks of their respective owners.

Copyright © 2021 Organon Global Inc.
All rights reserved.

Revised: 6/2021

usppi-og0462-t-tol-2106r000

PRINCIPAL DISPLAY PANEL - 10 mg Tablet Pouch Carton

Maxalt®
(rizatriptan benzoate)
10 mg
TABLETS

NDC 78206-142-01

Each tablet contains 14.53 mg of rizatriptan benzoate,
equivalent to 10 mg rizatriptan.

18 Tablets

USUAL DOSAGE:
See accompanying circular.

Rx only

Manuf. by:
Zhejiang Huahai Pharmaceutical Co., Ltd.
Xunqiao, Linhai, Zhejiang 317024, China
Dist. by: Organon LLC, a subsidiary of
ORGANON & Co.,
Jersey City, NJ 07302, USA
Rizatriptan benzoate (active ingred.) Made in Ireland.
Formulated in China.

PRINCIPAL DISPLAY PANEL - 10 mg Tablet Case Carton

Maxalt-MLT®
(rizatriptan benzoate)
ORALLY DISINTEGRATING TABLETS
10 mg

NDC 78206-143-01

Each tablet contains 14.53 mg of rizatriptan benzoate, equivalent to 10 mg rizatriptan.

Phenylketonurics: contains phenylalanine (a component of aspartame)
2.10 mg per 10-mg orally disintegrating tablet.

6 Carrying Cases, Each Containing
3 Orally Disintegrating Tablets

USUAL DOSAGE: See accompanying circular.
Rx only

Manuf. by: Catalent UK Swindon, Zydis Ltd.
Swindon, Wiltshire, SN5 8RU, UK

Dist. by: Organon LLC, a subsidiary of
ORGANON & Co.,
Jersey City, NJ 07302, USA

Rizatriptan benzoate (active ingred.) Made in Ireland. Formulated in UK.